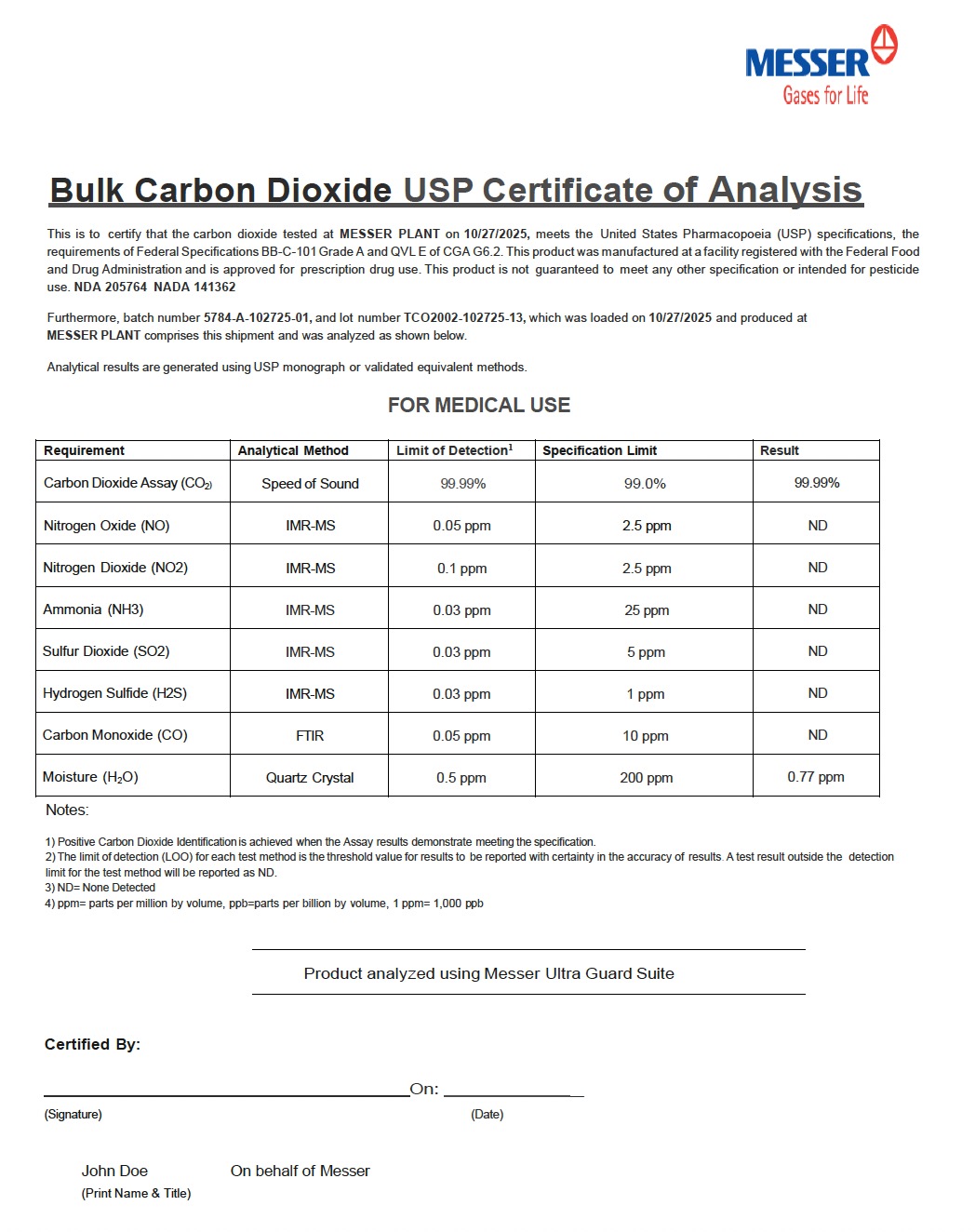 DRUG LABEL: Carbon Dioxide Refrigerated
NDC: 52438-014 | Form: GAS
Manufacturer: Messer LLC
Category: prescription | Type: HUMAN PRESCRIPTION DRUG LABEL
Date: 20260216

ACTIVE INGREDIENTS: CARBON DIOXIDE 990 mL/1 L

Messer LLC - Carbon Dioxide

PACKAGE LABEL

MESSER Gases for Life

Bulk Carbon Dioxide USP Certificate of Analysis

This is to certify that the carbon dioxide tested at MESSER PLANT on 10/27/2025, meets the United States Pharmacopoeia (USP) specifications, the requirements of Federal Specifications BB-C-101 Grade A and QVL E of CGA G6.2. This product was manufactured at a facility registered with the Federal Food and Drug Administration and is approved for prescription drug use. This product is not guaranteed to meet any other specification or intended for pesticide use. NDA 205764 NADA 141362

Furthermore, batch number 5784-A-102725-01, and lot number TCO2002-102725-13, which was loaded on 10/27/2025 and produced at MESSER PLANT comprises this shipment and was analyzed as shown below.

Analytical results are generated using USP monograph or validated equivalent methods.

FOR MEDICAL USE

Requirement Analytical Method Limit of Detection Specification Limit Result

Carbon Dioxide Assay (CO2) Speed of Sound 99.99 % 99.0 % 99.99%

Nitrogen Oxide (NO) IMR-MS 0.05 ppm 2.5 ppm ND

Nitrogen Dioxide (NO2) IMR-MS 0.1 ppm 2.5 ppm ND

Ammonia (NH3) IMR-MS 0.03 ppm 25 ppm ND

Sulfur Dioxide (SO2) IMR-MS 0.03 ppm 5 ppm ND

Hydrogen Sulfide (H2S) IMR-MS 0.03 ppm 1 ppm ND

Carbon Monoxide (CO) FTIR 0.05 ppm 10 ppm ND

Moisture (H2O) Quartz Crystal 0.5 ppm 200 ppm 0.77 ppm

Notes:

Positive Carbon Dioxide Identification is achieved when the Assay results demonstrate meeting the specification.
The limit of detection (LOD) for each test method is the threshold value for results to be reported with certainty in the accuracy of results. A test result outside the detection limit for the test method will be reported as ND.
ND = None Detected
ppm = parts per million by volume, ppb = parts per billion by volume, 1 ppm = 1,000 ppb

Product analyzed using Messer Ultra Guard Suite

Certified By:

(Signature) (Date)

John Doe
(Print Name & Title)

On behalf of Messer